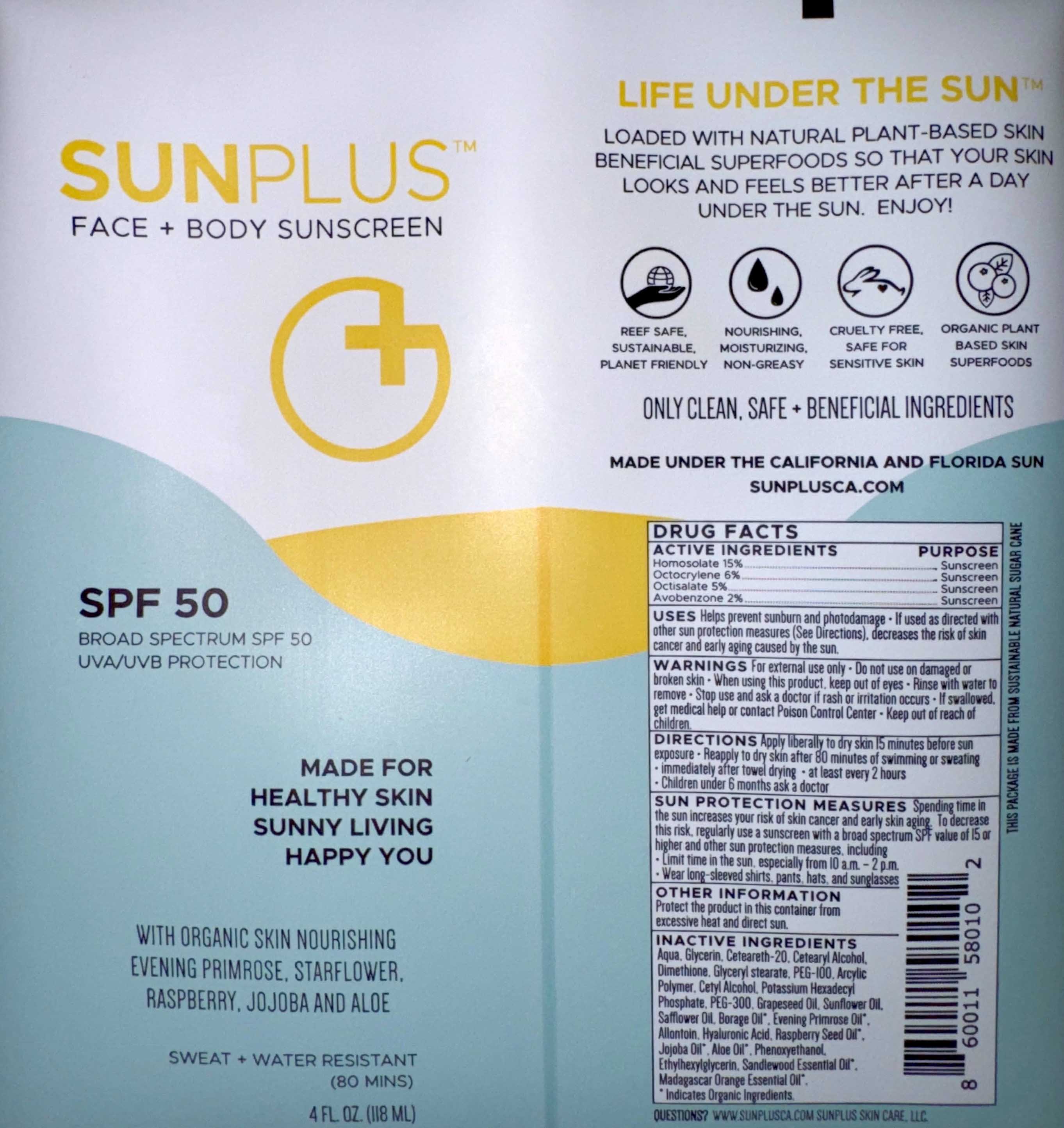 DRUG LABEL: Sunplus SPF50 Face  Body Sunscreen
NDC: 65112-304 | Form: LOTION
Manufacturer: I.Shay Cosmetics
Category: otc | Type: HUMAN OTC DRUG LABEL
Date: 20260204

ACTIVE INGREDIENTS: OCTOCRYLENE 0.06 g/118 mL; OCTISALATE 0.05 g/118 mL; AVOBENZONE 0.02 g/118 mL; HOMOSALATE 0.15 g/118 mL
INACTIVE INGREDIENTS: WATER

Sunplus SFP50 Face Body Sunscreen

ACTIVE INGREDIENT

Homosalate- 15%

Octocrylene- 6%

Octisalate- 5%

Avobenzone- 2%

PURPOSE

Sunscreen

WARNING - Keep out of reach of children

INDICATIONS AND USAGE

Helps prevent sunburn and photodamage.

If used as directed with other sun protection measures, decreases the risk of skin cancer and early aging caused by the sun.

INACTIVE INGREDIENT

Purified Water, Glycerin, Ceteareth-20, Cetearyl Alcohol, Dimethicone, Glyceryl stearate, PEG-100, Acrylic Polymer, Cetyl Alcohol, Potassium Hexadecyl Phosphate, PEG 300, Grapeseed Oil, Sunflower Oil, Safflower Oil, Organic Borage Oil, Organic Evening Primrose Oil, Allantoin, Hyaluronic Acid, Organic Raspberry Seed Oil, Organic Jojoba Oil, Organic Aloe Oil, Phenoxyethanol, Ethylhexylglycerin

WARNINGS

For external use only. Do not use on damaged or broken skin. When using this product keep out f eyes. Rinse with water to remove. Stop use and ask a doctor if rash or irritation occurs. If swallowed get medical help or contact Poison Control Center. Keep out of reach of children.

DOSAGE AND ADMINISTRATION

Apply liberally to dry skin 15 minutes before sun exposure. Reapply to dry skin after 80 minutes of swimming or sweating, immediately after towel drying, at least every 2 hours. Children under 6 months ask a doctor.